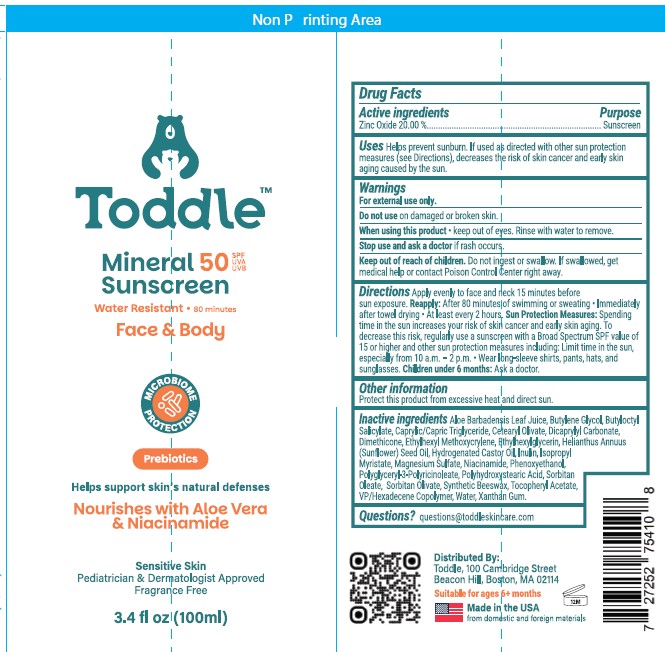 DRUG LABEL: SPF 50 Mineral Sunscreen Face and Body
NDC: 85865-002 | Form: LOTION
Manufacturer: Toddler Born Wild, Inc.
Category: otc | Type: HUMAN OTC DRUG LABEL
Date: 20251218

ACTIVE INGREDIENTS: ZINC OXIDE 20 g/100 mL
INACTIVE INGREDIENTS: MAGNESIUM SULFATE; NIACINAMIDE; DIMETHICONE; SORBITAN OLEATE; PHENOXYETHANOL; HYDROGENATED CASTOR OIL; HELIANTHUS ANNUUS (SUNFLOWER) SEED OIL; .ALPHA.-TOCOPHEROL ACETATE; VP/HEXADECENE COPOLYMER; INULIN; SYNTHETIC BEESWAX; ALOE BARBADENSIS LEAF JUICE; BUTYLOCTYL SALICYLATE; CAPRYLIC/CAPRIC TRIGLYCERIDE; DICAPRYLYL CARBONATE; ETHYLHEXYLGLYCERIN; ISOPROPYL MYRISTATE; WATER; BUTYLENE GLYCOL; ETHYLHEXYL METHOXYCRYLENE; XANTHAN GUM; SORBITAN OLIVATE; CETEARYL OLIVATE; POLYGLYCERYL-3 PENTARICINOLEATE; POLYHYDROXYSTEARIC ACID STEARATE

Toddle Mineral SPF 50 Sunscreen 1.7 fl oz,1.3 fl oz, and 6 fl oz

ACTIVE INGREDIENT

Zinc Oxide 20.00%

PURPOSE

Sunscreen

INDICATIONS AND USAGE

Helps prevent sunburn. If used as directed with other sun protection measures (See Directions), decreases the risk of skin cancer and early skin aging caused by the sun.

WARNINGS

For external use only

Do not use on damaged or broken skin.

When using this product keep out of eyes. Rinse with water to remove.

Keep out of reach of children. If swallowed, get medical help or contact Poison Control Center right away.

Stop use and ask a doctor if rash occurs.

DOSAGE AND ADMINISTRATION

Apply evenly to face and neck 15 minutes beofre sun exposure.

Reapply:

- After 40 minutes of swimming or sweating.
- Immediately after towel drying
- At least every 2 hours.

Sun Protection Measures:Spending time in the sun increases your risk of skin cancer and early skin aging. To decrease this risk, regularly use a sunscreen with a Broad Spectrum SPF value of 15 or higher and other sun protection measures including:

- Limin time in the sun, especially from 10a.m - 2p.m
- Wear long-sleeve shirts, pants, hats, and sunglasses.

Children under 6 months:Ask a doctor.

OTHER SAFETY INFORMATION

Protect this product from excessive heat and direct sun.

INACTIVE INGREDIENT

Aloe Barbadensis Leaf Juice

Butylene Glycol

Butyloctyl Salicylate

Caprylic/Capric Triglyceride

Cetearyl Olivate

Dicaprylyl Carbonate

Dimethicone

Ethylhexyl Methoxycrylene

Ethylhexylglycerin

Helianthus Annuus (Sunflower) Seed Oil

Hydrogenated Castor Oil

Inulin

Isopropyl Myristate

Magnesium Sulfate

Niacinamide

Phenoxyethanol

Polyglyceryl-3 Polyricinoleate

Polyhydroxystearic Acid

Sorbitan Oleate

Sorbitan Olivate

Synthetic Beeswax

Tocopheryl Acetate

VP/Hexadecene Copolymer

Water

Xanthan Gum

Questions?

questions@toddleskincare.com